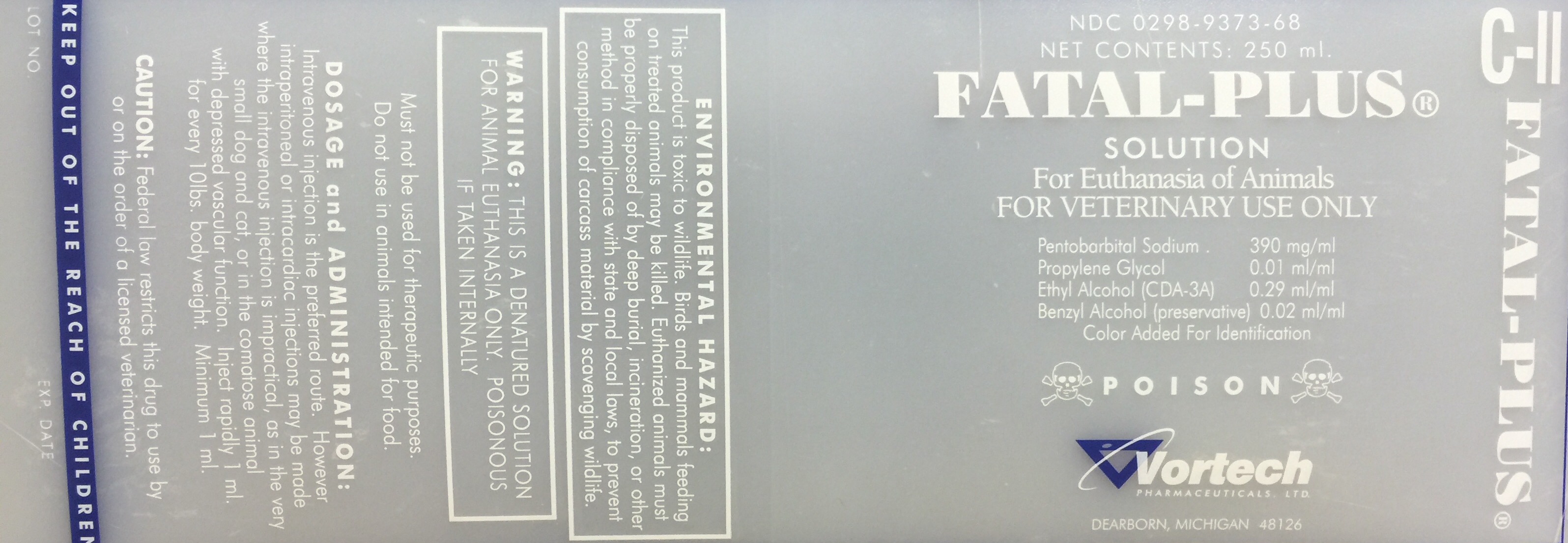 DRUG LABEL: Fatal-Plus Solution
                        
NDC: 0298-9373 | Form: INJECTION, SOLUTION
Manufacturer: Vortech Pharmaceuticals, Ltd.
Category: animal | Type: PRESCRIPTION ANIMAL DRUG LABEL
Date: 20161221
DEA Schedule: CII

ACTIVE INGREDIENTS: Pentobarbital Sodium 390 mg/1 mL

Description

Fatal-Plus Solution

FOR VETERINARY USE ONLY

For Euthanasia of Animals

DOSAGE AND ADMINISTRATION:

Intravenous injection is the preferred route. However, intraperitoneal or intracardiac injections may be made where the intravenous injection is impractical, as in the very small dog and cat, or in the comatose animal with depressed vascular function. Inject rapidly 1 mL for every 10 lbs. body weight Minimum 1 mL.

WARNING: THIS IS A DENATURED SOLUTION FOR ANIMAL EUTHANASIA ONLY. POISONOUS IF TAKEN INTERNALLY. Must not be used for therapeutic purposes. Do not use in animals intended for food.

ENVIRONMENTAL HAZARD:

This product is toxic to wildlife. Birds and mammals feeding on treated animals may be killed. Birds and mammals feeding on treated animals may be killed. Euthanized animals must be properly disposed of by deep burial, incineration, or other method in compliance with state and local laws, to prevent consumption of carcass material by scavenging wildlife.

CAUTION: Federal law restricts this drug to use by or on the order of a licensed veterinarian.

POISON: KEEP OUT OF THE REACH OF CHILDREN

Principle Display Panel

Fatal-Plus Solution - NDC: 0298-9373-68

FOR VETERINARY USE ONLY

For Euthanasia of Animals

DOSAGE AND ADMINISTRATION:

Intravenous injection is the preferred route. However, intraperitoneal or intracardiac injections may be made where the intravenous injection is impractical, as in the very small dog and cat, or in the comatose animal with depressed vascular function. Inject rapidly 1 mL for every 10 lbs. body weight Minimum 1 mL.

WARNING: THIS IS A DENATURED SOLUTION FOR ANIMAL EUTHANASIA ONLY. POISONOUS IF TAKEN INTERNALLY. Must not be used for therapeutic purposes. Do not use in animals intended for food.

ENVIRONMENTAL HAZARD:

This product is toxic to wildlife. Birds and mammals feeding on treated animals may be killed. Birds and mammals feeding on treated animals may be killed. Euthanized animals must be properly disposed of by deep burial, incineration, or other method in compliance with state and local laws, to prevent consumption of carcass material by scavenging wildlife.

CAUTION: Federal law restricts this drug to use by or on the order of a licensed veterinarian.

POISON: KEEP OUT OF THE REACH OF CHILDREN